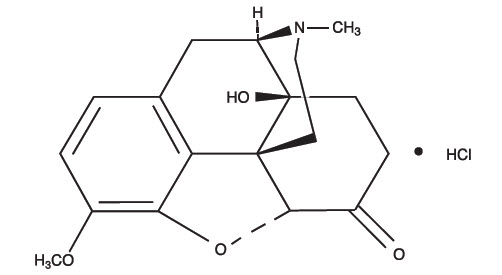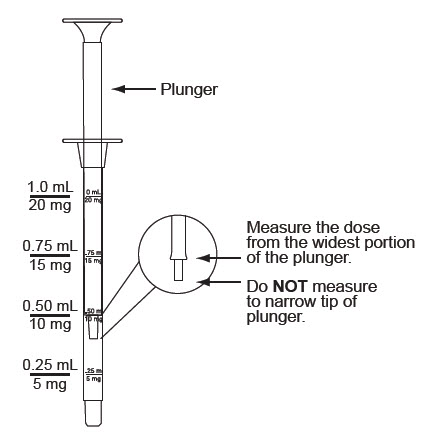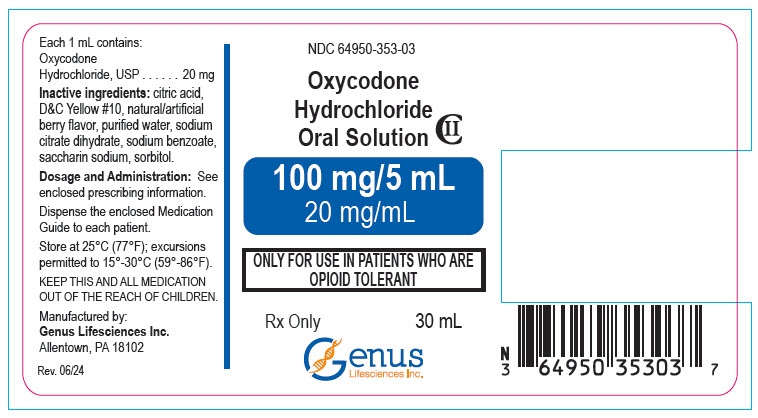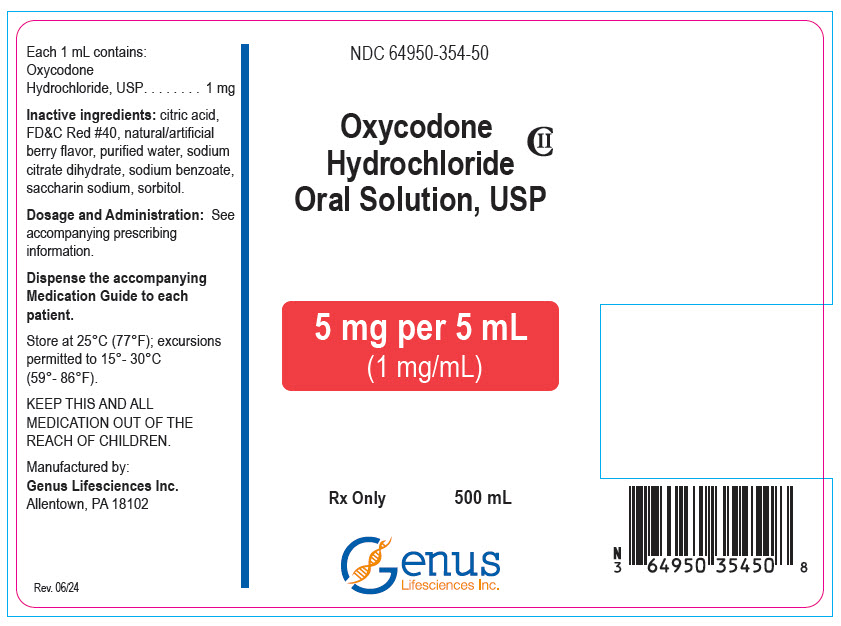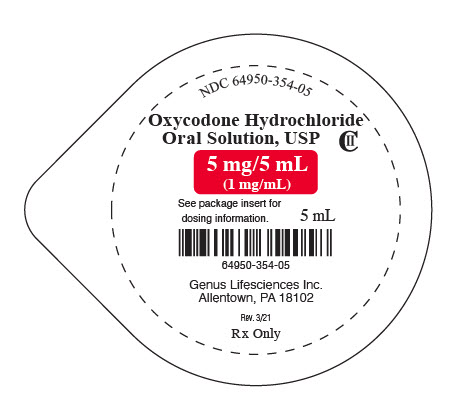 DRUG LABEL: Oxycodone Hydrochloride
NDC: 67296-2167 | Form: SOLUTION
Manufacturer: Redpharm Drug
Category: prescription | Type: HUMAN PRESCRIPTION DRUG LABEL
Date: 20251211
DEA Schedule: CII

ACTIVE INGREDIENTS: OXYCODONE HYDROCHLORIDE 5 mg/5 mL
INACTIVE INGREDIENTS: FD&C RED NO. 40; ANHYDROUS CITRIC ACID; WATER; TRISODIUM CITRATE DIHYDRATE; SODIUM BENZOATE; SACCHARIN SODIUM; SORBITOL

HIGHLIGHTS OF PRESCRIBING INFORMATION

These highlights do not include all the information needed to use OXYCODONE HYDROCHLORIDE ORAL SOLUTION safely and effectively. See full prescribing information for OXYCODONE HYDROCHLORIDE ORAL SOLUTION.
Oxycodone Hydrochloride oral solution CII
Initial U.S. Approval: 1950

WARNING: SERIOUS AND LIFE-THREATENING RISKS FROM USE OF OXYCODONE HYDROCHLORIDE ORAL SOLUTION

WARNING: SERIOUS AND LIFE-THREATENING RISKS FROM USE OF OXYCODONE HYDROCHLORIDE SOLUTION

See full prescribing information for complete boxed warning.

- Ensure accuracy when prescribing, dispensing, and administering Oxycodone Hydrochloride Oral Solution. Dosing errors due to confusion between mg and mL, and other oxycodone hydrochloride oral solutions of different concentrations can result in accidental overdose and death (2.1, 5.1).
- Oxycodone Hydrochloride Oral Solution exposes users to risks of addiction, abuse, and misuse, which can lead to overdose and death. Assess patient's risk before prescribing and reassess regularly for these behaviors and conditions (5.2)
- Serious, life-threatening, or fatal respiratory depression may occur, especially during initiation or following a dosage increase. To reduce risk of respiratory depression, proper dosing and titration of Oxycodone Hydrochloride Oral Solution are essential. (5.3)
- Accidental ingestion of Oxycodone Hydrochloride Oral Solution, especially by children, can result in a fatal overdose of oxycodone. (5.3)
- Concomitant use of opioids with benzodiazepines or other central nervous system (CNS) depressants, including alcohol, may result in profound sedation, respiratory depression, coma, and death. Reserve concomitant prescribing for use in patients for whom alternative treatment options are inadequate. (5.4, 7)
- If opioid use is required for an extended period of time in a pregnant woman, advise the patient of the risk of Neonatal Opioid Withdrawal Syndrome, which may be life-threatening if not recognized and treated. Ensure that management by neonatology experts will be available at delivery. (5.5)
- Healthcare providers are strongly encouraged to complete a REMS-compliant education program and to counsel patients and caregivers on serious risks, safe use, and the importance of reading the Medication Guide with each prescription. (5.6)
- The concomitant use with CYP3A4 inhibitors (or discontinuation of CYP3A4 inducers) can result in a fatal overdose of oxycodone. (5.77, 12.3)

RECENT MAJOR CHANGES

Boxed Warning | 12/2023
Indications and Usage (1) | 12/2023
Dosage and Administration (2.1, 2.3, 2.4) | 12/2023
Warnings and Precautions (5.8) | 12/2023

1 INDICATIONS AND USAGE

Oxycodone Hydrochloride Oral Solution is an opioid agonist indicated in adults for the management of pain severe enough to require an opioid analgesic and for which alternative treatments are inadequate. (1)

Oxycodone Hydrochloride Oral Solution 100 mg per 5 mL (20 mg/mL) is indicated for the relief of pain in opioid-tolerant adults.

Limitations of Use (1)

Because of the risks of addiction, abuse, and misuse with opioids, which can occur at any dosage or duration (5.2), reserve Oxycodone Hydrochloride Oral Solution for use in patients for whom alternative treatment options (e.g., non-opioid analgesics or opioid combination products):

- Have not been tolerated or are not expected to be tolerated,
- Have not provided adequate analgesia or are not expected to provide adequate analgesia

Oxycodone Hydrochloride Oral Solution should not be used for an extended period of time unless the pain remains severe enough to require an opioid analgesic and for which alternative treatment options continue to be inadequate.

2 DOSAGE AND ADMINISTRATION

- Oxycodone Hydrochloride Oral Solution should be prescribed only by healthcare professionals who are knowledgeable about the use of opioids and how to mitigate the associated risks. (2.1)
- Use the lowest effective dosage for the shortest duration of time consistent with individual patient treatment goals. Reserve titration to higher doses of Oxycodone Hydrochloride Oral Solution for patients in whom lower doses are insufficiently effective and in whom the expected benefits of using a higher dose opioid clearly outweigh the substantial risks. (2.1, 5)
- Many acute pain conditions (e.g., the pain that occurs with a number of surgical procedures or acute musculoskeletal injuries) require no more than a few days of an opioid analgesic. Clinical guidelines on opioid prescribing for some acute pain conditions are available. (2.1)
- Initiate the dosing regimen for each patient individually, taking into account the patient's underlying cause and severity of pain, prior analgesic treatment and response, and risk factors for addiction, abuse and misuse. (2.1, 5.2)
- Respiratory depression can occur at any time during opioid therapy, especially when initiating and following dosage increases with Oxycodone Hydrochloride Oral Solution. Consider this risk when selecting an initial dose and when making dose adjustments. (2.1, 5.3)
- Discuss availability of naloxone with the patient and caregiver and assess each patient's need for access to naloxone, both when initiating and renewing treatment with Oxycodone Hydrochloride Oral Solution. Consider prescribing naloxone based on the patient's risk factors for overdose (2.2, 5.2, 5.3, 5.4).
- Initiate dosing with a range of 5 to 15 mg every 4 to 6 hours as needed for pain, and at the lowest dose necessary to achieve adequate analgesia. Titrate the dose based upon the individual patient's response to their initial dose of Oxycodone Hydrochloride Oral Solution. (2.3, 2.4)
- Do not abruptly discontinue Oxycodone Hydrochloride Oral Solution in a physically dependent patient because rapid discontinuation of opioid analgesics has resulted in serious withdrawal symptoms, uncontrolled pain, and suicide. (2.5, 5.15)

3 DOSAGE FORMS AND STRENGTHS

Oral Solution

- 5 mg per 5 mL (1 mg/mL)
- 100 mg per 5 mL (20 mg/mL) (3)

4 CONTRAINDICATIONS

- Significant respiratory depression (4)
- Acute or severe bronchial asthma in an unmonitored setting in absence of resuscitative equipment. (4)
- Known or suspected gastrointestinal obstruction, including paralytic ileus. (4)
- Hypersensitivity to oxycodone. (4)

5 WARNINGS AND PRECAUTIONS

- Opioid-Induced Hyperalgesia and Allodynia: Opioid-Induced Hyperalgesia (OIH) occurs when an opioid analgesic paradoxically causes an increase in pain, or an increase in sensitivity to pain. If OIH is suspected, carefully consider appropriately decreasing the dose of the current opioid analgesic or opioid rotation. (5.8)
- Life-Threatening Respiratory Depression in Patients with Chronic Pulmonary Disease or in Elderly, Cachectic or Debilitated Patients: Regularly evaluate, particularly during initiation and titration. (5.9)
- Adrenal Insufficiency: If diagnosed, treat with physiologic replacement of corticosteroids, and wean patient off of the opioid. (5.10)
- Severe Hypotension: Regularly evaluate during dosage initiation and titration. Avoid use of Oxycodone Hydrochloride Oral Solution in patients with circulatory shock. (5.11)
- Risks of Use in Patients with Increased lntracranial Pressure, Brain Tumors, Head Injury or Impaired Consciousness: Monitor for sedation and respiratory depression. Avoid use of Oxycodone Hydrochloride Oral Solution in patients with impaired consciousness or coma. (5.12)

6 ADVERSE REACTIONS

Most common adverse reactions are nausea, constipation, vomiting, headache, pruritus, insomnia, dizziness, asthenia, and somnolence. (6)

To report SUSPECTED ADVERSE REACTIONS, contact Allucent at 1- 866-511-6754 or FDA at 1-800-FDA-1088 or www.fda.gov.medwatch.

7 DRUG INTERACTIONS

- Serotonergic Drugs: Concomitant use may result in serotonin syndrome. Discontinue Oxycodone Hydrochloride Oral Solution if serotonin syndrome is suspected. (7)
- Monoamine Oxidase Inhibitors (MAOIs): Can potentiate the effects of oxycodone. Avoid concomitant use in patients receiving MAOIs or within 14 days of stopping treatment with an MAOI. (7)
- Mixed Agonist/Antagonist and Partial Agonist Opioid Analgesics:Avoid use with Oxycodone Hydrochloride Oral Solution because they may reduce analgesic effect of Oxycodone Hydrochloride Oral Solution or precipitate withdrawal symptoms. (7)

8 USE IN SPECIFIC POPULATIONS

- Pregnancy:May cause fetal harm. (8.1)

FULL PRESCRIBING INFORMATION

WARNING: SERIOUS AND LIFE-THREATENING RISKS FROM USE OF OXYCODONE HYDROCHLORIDE ORAL SOLUTION

Risk of Medication Errors

Ensure accuracy when prescribing, dispensing, and administering Oxycodone Hydrochloride Oral Solution. Dosing errors due to confusion between mg and mL, and other oxycodone hydrochloride oral solutions of different concentrations can result in accidental overdose and death [see Dosage and Administration (2.1), Warnings and Precautions (5.1)] .

Addiction, Abuse, and Misuse

Because the use of Oxycodone Hydrochloride Oral Solution exposes patients and other users to the risks of opioid addiction, abuse, and misuse, which can lead to overdose and death, assess each patient's risk prior to prescribing and reassess all patients regularly for the development of these behaviors and conditions [see Warnings and Precautions (5.2)] .

Life-Threatening Respiratory Depression

Serious, life-threatening, or fatal respiratory depression may occur with use of Oxycodone Hydrochloride Oral Solution, especially during initiation or following a dosage increase. To reduce the risk of respiratory depression, especially during initiation or following a dose increase. To reduce the risk of respiratory depression, proper dosing and titration of Oxycodone Hydrochloride Oral Solution are essential [see Warnings and Precautions (5.3)].

Accidental Ingestion

Accidental ingestion of even one dose of Oxycodone Hydrochloride Oral Solution, especially by children, can result in a fatal overdose of oxycodone [see Warnings and Precautions (5.3)] .

Risks From Concomitant Use With Benzodiazepines Or Other CNS Depressants

Concomitant use of opioids with benzodiazepines or other central nervous system (CNS) depressants, including alcohol, may result in profound sedation, respiratory depression, coma, and death. Reserve concomitant prescribing of Oxycodone Hydrochloride Oral Solution and benzodiazepines or other CNS depressants for use in patients for whom alternative treatment options are inadequate [see Warnings and Precautions (5.4), Drug Interactions (7)].

Neonatal Opioid Withdrawal Syndrome (NOWS)

If opioid use is required for an extended period of time in a pregnant woman, advise the patient of the risk of NOWS, which may be life-threatening if not recognized and treated. Ensure that management by neonatology experts will be available at delivery [see Warnings and Precautions (5.5)] .

Opioid Analgesic Risk Evaluation and Mitigation Strategy (REMS)

Healthcare providers are strongly encouraged to complete a REMS-compliant education program and to counsel patients and caregivers on serious risks, safe use, and the importance of reading the Medication Guide with each prescription [see Warnings and Precautions (5.6)].

Cytochrome P450 3A4 Interaction

The concomitant use of Oxycodone Hydrochloride Oral Solution with all cytochrome P450 3A4 inhibitors may result in an increase in oxycodone plasma concentrations, which could increase or prolong adverse reactions and may cause potentially fatal respiratory depression. In addition, discontinuation of a concomitantly used cytochrome P450 3A4 inducer may result in an increase in oxycodone plasma concentration. Regularly evaluate patients receiving Oxycodone Hydrochloride Oral Solution and any CYP3A4 inhibitor or inducer [see Warnings and Precautions (5.7 Drug Interactions (7), Clinical Pharmacology (12.3)].

1 INDICATIONS AND USAGE

Oxycodone Hydrochloride Oral Solution is indicated in adults for the management of pain severe enough to require an opioid analgesic and for which alternative treatments are inadequate.

Oxycodone Hydrochloride Oral Solution 100 mg per 5 mL (20 mg/mL) is indicated for the relief of pain in opioid-tolerant adults.

Limitations of Use

Because of the risks of addiction, abuse, and misuse with opioids, which can occur at any dosage or duration [see Warnings and Precautions (5.2)] , reserve Oxycodone Hydrochloride Oral Solution for use in patients for whom alternative treatment options [e.g., non-opioid analgesics or opioid combination products]:

- Have not been tolerated or are not expected to be tolerated
- Have not provided adequate analgesia or are not expected to provide adequate analgesia.

Oxycodone Hydrochloride Oral Solution should not be used for an extended period of time unless the pain remains severe enough to require an opioid analgesic and for which alternative treatment options continue to be inadequate.

2 DOSAGE AND ADMINISTRATION

2.1 Important Dosage and Administration Instructions

Oxycodone Hydrochloride Oral Solution is available in two concentrations: 5 mg per 5 mL (1 mg/mL), and 100 mg per 5 mL (20 mg/mL). Oxycodone Hydrochloride Oral Solution 100 mg per 5 mL (20 mg/mL) is for use in only opioid-tolerant patientswho have already been receiving opioid therapy. Use this strength only for patients who have already been titrated to a stable analgesic regimen using lower strengths of oxycodone hydrochloride and who can benefit from use of a smaller volume of oral solution.

Patients considered to be opioid tolerant are those who are receiving, for one week or longer, at least 60 mg oral morphine per day, 25 mcg transdermal fentanyl per hour, 30 mg oral oxycodone per day, 8 mg oral hydromorphone per day, 25 mg oral oxymorphone per day, 60 mg oral hydrocodone per day, or an equianalgesic dose of another opioid.

Ensure accuracy when prescribing, dispensing, and administering Oxycodone Hydrochloride Oral Solution to avoid dosing errors due to confusion between mg and mL, and with other oxycodone hydrochloride solutions of different concentrations, which could result in accidental overdose and death. Ensure the proper dose is communicated and dispensed. When writing prescriptions, include both the total dose in mg and the total dose in volume.

Instruct patients and caregivers on how to accurately measure and take or administer the correct dose of Oxycodone Hydrochloride Oral Solution.

Strongly advise patients and caregivers to always use the enclosedgraduated measuring cup when administering Oxycodone Hydrochloride Oral Solution 5 mg per 5 mL and always use the enclosedgraduated oral syringe when administering Oxycodone Hydrochloride Oral Solution 100 mg per 5 mL (20 mg per mL) to ensure that the dose is measured and administered accurately.

Instruct patients and caregivers to never use household teaspoons or tablespoons to measure Oxycodone Hydrochloride Oral Solution.

- Oxycodone Hydrocodone Oral Solution should be prescribed only by healthcare professionals who are knowledgeable about the use of opioids and how to mitigate the associated risks.
- Use the lowest effective dosage for the shortest duration of time consistent with individual patient treatment goals [see Warnings and Precautions (5)]. Because the risk of overdose increases as opioid doses increase, reserve titration to higher doses of Oxycodone Hydrochloride Oral Solution for patients in whom lower doses are insufficiently effective and in whom the expected benefits of using a higher dose opioid clearly outweigh the substantial risks.
- Many acute pain conditions (e.g., the pain that occurs with a number of surgical procedures or acute musculoskeletal injuries) require no more than a few days of an opioid analgesic. Clinical guidelines on opioid prescribing for some acute pain conditions are available.
- There is variability in the opioid analgesic dose and duration needed to adequately manage pain due both to the cause of pain and to individual patient factors. Initiate the dosing regimen for each patient individually, taking into account the patient's underlying cause and severity of pain, prior analgesic treatment and response, and risk factors for addiction, abuse, and misuse [see Warnings and Precautions (5.2)].
- Respiratory depression can occur at any time during opioid therapy, especially when initiating and following dosage increases with Oxycodone Hydrochloride Oral Solution. Consider this risk when selecting an initial dose and when making dose adjustments [see Warnings and Precautions (5)].

2.2 Patient Access to Naloxone for the Emergency Treatment of Opioid Overdose

Discuss the availability of naloxone for the emergency treatment of opioid overdose with the patient and caregiver and assess the potential need for access to naloxone, both when initiating and renewing treatment with Oxycodone Hydrochloride Oral Solution [see Warnings and Precautions (5.3)].

Inform patients and caregivers about the various ways to obtain naloxone as permitted by individual state naloxone dispensing and prescribing requirements or guidelines (e.g., by prescription, directly from a pharmacist, or as part of a community-based program).

Consider prescribing naloxone, based on the patient's risk factors for overdose, such as concomitant use of CNS depressants, a history of opioid use disorder, or prior opioid overdose. The presence of risk factors for overdose should not prevent the proper management of pain in any given patient [see Warnings and Precautions (5.2, 5.3, 5.4].

Consider prescribing naloxone if the patient has household members (including children) or other close contacts at risk for accidental ingestion or overdose.

2.3 Initial Dosage

Although it is not possible to list every condition that is important to the selection of the initial dose of Oxycodone Hydrochloride Oral Solution, attention must be given to:

1. the daily dose, potency and characteristics of a full agonist or mixed agonist/antagonist the patient has been taking previously
2. the reliability of the relative potency estimate to calculate the dose of oxycodone HCl needed
3. the degree of opioid tolerance
4. the general condition and medical status of the patient, including the patient's weight and age
5. the balance between pain management and adverse reactions
6. the type and severity of the patient's pain
7. risk factors for abuse or addiction, including a prior history of abuse or addiction

Use of Oxycodone Hydrochloride Oral Solution as the First Opioid Analgesic

Do not initiate treatment with Oxycodone Hydrochloride Oral Solution 100 mg per 5 mL (20 mg per mL) in patients who are opioid naïve. Select an alternate product with lower concentration.

Initiate treatment with Oxycodone Hydrochloride Oral Solution in a dosing range of 5 to 15 mg every 4 to 6 hours as needed for pain, and at the lowest dose necessary to achieve adequate analgesia. Titrate the dose based upon the individual patient's response to their initial dose of Oxycodone Hydrochloride Oral Solution.

Conversion from Other Opioids to Oxycodone Hydrochloride Oral Solution

There is inter-patient variability in the potency of opioid drugs and opioid formulations. Therefore, a conservative approach is advised when determining the total daily dosage of Oxycodone Hydrochloride Oral Solution. It is safer to underestimate a patient's 24-hour Oxycodone Hydrochloride Oral Solution dosage than to overestimate the 24-hour Oxycodone Hydrochloride Oral Solution dosage and manage an adverse reaction due to overdose. If a patient has been receiving opioid-containing medications prior to taking Oxycodone Hydrochloride Oral Solution, the potency of the prior opioid relative to oxycodone should be factored into the selection of the total daily dose (TDD) of oxycodone.

In converting patients from other opioids to Oxycodone Hydrochloride Oral Solution close observation and adjustment of dosage based upon the patient's response to Oxycodone Hydrochloride Oral Solution is imperative. Administration of supplemental analgesia for breakthrough or incident pain and titration of the total daily dose of Oxycodone Hydrochloride Oral Solution may be necessary, especially in patients who have disease states that are changing rapidly.

Conversion from Oxycodone Hydrochloride Oral Solution to Extended-Release Oxycodone Hydrochloride

The relative bioavailability of Oxycodone Hydrochloride Oral Solution compared to extended-release oxycodone is unknown, so conversion to extended-release oxycodone may lead to increased risk of excessive sedation and respiratory depression.

2.4 Titration and Maintenance of Therapy

Individually titrate Oxycodone Hydrochloride Oral Solution to a dose that provides adequate analgesia and minimizes adverse reactions. Continually reevaluate patients receiving Oxycodone Hydrochloride Oral Solution to assess the maintenance of pain control, signs and symptoms of opioid withdrawal, and other adverse reactions, as well as to reassess for the development of addiction, abuse, or misuse [see Warnings and Precautions (5.2, 5.15)].

Frequent communication is important among the prescriber, other members of the healthcare team, the patient, and the caregiver/family during periods of changing analgesic requirements, including initial titration.

If the level of pain increases after dosage stabilization, attempt to identify the source of increased pain before increasing the Oxycodone Hydrochloride Oral Solution dosage. If after increasing the dosage, unacceptable opioid-related adverse reactions are observed (including an increase in pain after a dosage increase), consider reducing the dosage [see Warnings and Precautions (5)] . Adjust the dosage to obtain an appropriate balance between management of pain and opioid-related adverse reactions.

2.5 Safe Reduction or Discontinuation of Oxycodone Hydrochloride Oral Solution

Do not abruptly discontinue Oxycodone Hydrochloride Oral Solution in patients who may be physically dependent on opioids. Rapid discontinuation of opioid analgesics in patients who are physically dependent on opioids has resulted in serious withdrawal symptoms, uncontrolled pain, and suicide. Rapid discontinuation has also been associated with attempts to find other sources of opioid analgesics, which may be confused with drug-seeking for abuse. Patients may also attempt to treat their pain or withdrawal symptoms with illicit opioids, such as heroin, and other substances.

When a decision has been made to decrease the dose or discontinue therapy in an opioid-dependent patient taking Oxycodone Hydrochloride Oral Solution, there are a variety of factors that should be considered, including the total daily dose of opioid (including Oxycodone Hydrochloride Oral Solution) the patient has been taking, the duration of treatment, the type of pain being treated, and the physical and psychological attributes of the patient. It is important to ensure ongoing care of the patient and to agree on an appropriate tapering schedule and follow-up plan so that patient and provider goals and expectations are clear and realistic. When opioid analgesics are being discontinued due to a suspected substance use disorder, evaluate and treat the patient, or refer for evaluation and treatment of the substance use disorder. Treatment should include evidence-based approaches, such as medication assisted treatment of opioid use disorder.

Complex patients with co-morbid pain and substance use disorders may benefit from referral to a specialist.

There are no standard opioid tapering schedules that are suitable for all patients. Good clinical practice dictates a patient-specific plan to taper the dose of the opioid gradually. For patients on Oxycodone Hydrochloride Oral Solution who are physically opioid-dependent, initiate the taper by a small enough increment (e.g., no greater than 10% to 25% of the total daily dose) to avoid withdrawal symptoms, and proceed with dose-lowering at an interval of every 2 to 4 weeks. Patients who have been taking opioids for briefer periods of time may tolerate a more rapid taper.

It may be necessary to provide the patient with lower dosage strengths to accomplish a successful taper. Reassess the patient frequently to manage pain and withdrawal symptoms, should they emerge. Common withdrawal symptoms include restlessness, lacrimation, rhinorrhea, yawning, perspiration, chills, myalgia, and mydriasis. Other signs and symptoms also may develop, including irritability, anxiety, backache, joint pain, weakness, abdominal cramps, insomnia, nausea, anorexia, vomiting, diarrhea, or increased blood pressure, respiratory rate, or heart rate. If withdrawal symptoms arise, it may be necessary to pause the taper for a period of time or raise the dose of the opioid analgesic to the previous dose, and then proceed with a slower taper. In addition, evaluate patients for any changes in mood, emergence of suicidal thoughts, or use of other substances.

When managing patients taking opioid analgesics, particularly those who have been treated for an extended period of time, and/or with high doses for chronic pain, ensure that a multimodal approach to pain management, including mental health support (if needed), is in place prior to initiating an opioid analgesic taper. A multimodal approach to pain management may optimize the treatment of chronic pain, as well as assist with the successful tapering of the opioid analgesic [see Warnings and Precautions (5.15), Drug Abuse and Dependence (9.3)]

3 DOSAGE FORMS AND STRENGTHS

Oxycodone Hydrochloride Oral Solution, USP

5 mg per 5 mL (1 mg/mL) Strength Oral Solution: Each 5 mL of red Oxycodone Hydrochloride Oral Solution, USP contains oxycodone hydrochloride 5 mg.

100 mg per 5 mL (20 mg per mL) Strength Oral Solution: Each 5 mL of yellow Oxycodone Hydrochloride Oral Solution, USP contains oxycodone hydrochloride 100 mg.

4 CONTRAINDICATIONS

Oxycodone Hydrochloride Oral Solution is contraindicated in patients with:

- Significant respiratory depression [see Warnings and Precautions (5.3)]
- Acute or severe bronchial asthma in an unmonitored setting or in the absence of resuscitative equipment [see Warnings and Precautions (5.9)]
- Known or suspected gastrointestinal obstruction, including paralytic ileus [see Warnings and Precautions (5.13)]
- Hypersensitivity to oxycodone (e.g., angioedema) [see Adverse Reactions (6)]

5 WARNINGS AND PRECAUTIONS

5.1 Risk of Accidental Overdose and Death due to Medication Errors

Dosing errors can result in accidental overdose and death. Avoid dosing errors that may result from confusion between mg and mL and confusion with oxycodone hydrochloride solutions of different concentrations, when prescribing, dispensing, and administering Oxycodone Hydrochloride Oral Solution. Ensure that the dose is communicated clearly and dispensed accurately.

Instruct patients and caregivers on how to measure and take or administer the correct dose of Oxycodone Hydrochloride Oral Solution and to use extreme caution when measuring the dose. Instruct patients and caregivers to always use the enclosedgraduated measuring cup when administering Oxycodone Hydrochloride Oral Solution 5 mg per 5 mL (1 mg/mL) and always use the enclosedgraduated oral syringe when administering Oxycodone Hydrochloride Oral Solution 100 mg per 5 mL (20 mg/ mL) to ensure the dose is measured and administered accurately. Instruct them to never use a teaspoon or a tablespoon to measure a dose because household teaspoons or tablespoon are not adequate measuring devices.

5.2 Addiction, Abuse, and Misuse

Oxycodone Hydrochloride Oral Solution contains oxycodone, a Schedule II controlled substance. As an opioid, Oxycodone Hydrochloride Oral Solution exposes users to the risks of addiction, abuse, and misuse [see Drug Abuse and Dependence (9)].

Although the risk of addiction in any individual is unknown, it can occur in patients appropriately prescribed Oxycodone Hydrochloride Oral Solution. Addiction can occur at recommended dosages and if the drug is misused or abused.

Assess each patient's risk for opioid addiction, abuse, or misuse prior to prescribing Oxycodone Hydrochloride Oral Solution, and reassess all patients receiving Oxycodone Hydrochloride Oral Solution for the development of these behaviors and conditions. Risks are increased in patients with a personal or family history of substance abuse (including drug or alcohol abuse or addiction) or mental illness (e.g., major depression). The potential for these risks should not, however, prevent the proper management of pain in any given patient. Patients at increased risk may be prescribed opioids such as Oxycodone Hydrochloride Oral Solution but use in such patients necessitates intensive counseling about the risks and proper use of Oxycodone Hydrochloride Oral Solution along with frequent reevaluation for signs of addiction, abuse, and misuse. Consider prescribing naloxone for the emergency treatment of opioid overdose [see Dosage and Administration (2.2), Warnings and Precautions (5.3)].

Opioids are sought for nonmedical use and are subject to diversion from legitimate prescribed use. Consider these risks when prescribing or dispensing Oxycodone Hydrochloride Oral Solution. Strategies to reduce these risks include prescribing the drug in the smallest appropriate quantity and advising the patient on careful storage of the drug during the course of treatment and on the proper disposal of unused drug. Contact local state professional licensing board or state-controlled substances authority for information on how to prevent and detect abuse or diversion of this product.

5.3 Life-Threatening Respiratory Depression

Serious, life-threatening, or fatal respiratory depression has been reported with the use of opioids, even when used as recommended. Respiratory depression, if not immediately recognized and treated, may lead to respiratory arrest and death. Management of respiratory depression may include close observation, supportive measures, and use of opioid antagonists, depending on the patient's clinical status [see Overdosage (10)]. Carbon dioxide (C02) retention from opioid-induced respiratory depression can exacerbate the sedating effects of opioids.

While serious, life-threatening, or fatal respiratory depression can occur at any time during the use of Oxycodone Hydrochloride Oral Solution, the risk is greatest during the initiation of therapy or following a dosage increase.

To reduce the risk of respiratory depression, proper dosing and titration of Oxycodone Hydrochloride Oral Solution are essential [see Dosage and Administration (2)] . Over estimating the Oxycodone Hydrochloride Oral Solution dosage when converting patients from another opioid product can result in a fatal overdose with the first dose. Oxycodone Hydrochloride Oral Solution 100 mg per 5 mL (20 mg/mL) is for use in opioid-tolerant patients only. Administration of this formulation may cause fatal respiratory depression when administered to patients who are not tolerant to the respiratory depressant effects of opioids.

Accidental ingestion of even one dose of Oxycodone Hydrochloride Oral Solution, especially by children, can result in respiratory depression and death due to an overdose of oxycodone.

Educate patients and caregivers on how to recognize respiratory depression and emphasize the importance of calling 911 or getting emergency medical help right away in the event of a known or suspected overdose .

Opioids can cause sleep-related breathing disorders including central sleep apnea (CSA) and sleep-related hypoxemia. Opioid use increases the risk of CSA in a dose-dependent fashion. In patients who present with CSA, consider decreasing the opioid dosage using best practices for opioid taper [see Dosage and Administration (2.5)].

Patient Access to Naloxone for the Emergency Treatment of Opioid Overdose

Discuss the availability of naloxone for the emergency treatment of opioid overdose with the patient and caregiver and assess the potential need for access to naloxone, both when initiating and renewing treatment with Oxycodone Hydrochloride Oral Solution. Inform patients and caregivers about the various ways to obtain naloxone as permitted by individual state naloxone dispensing and prescribing requirements or guidelines (e.g., by prescription, directly from a pharmacist, or as part of a community-based program). Educate patients and caregivers on how to recognize respiratory depression and emphasize the importance of calling 911 or getting emergency medical help, even if naloxone is administered .

Consider prescribing naloxone, based on the patient's risk factors for overdose, such as concomitant use of CNS depressants, a history of opioid use disorder, or prior opioid overdose. The presence of risk factors for overdose should not prevent the proper management of pain in any given patient. Also consider prescribing naloxone if the patient has household members (including children) or other close contacts at risk for accidental ingestion or overdose. If naloxone is prescribed, educate patients and caregivers on how to treat with naloxone. [see Dosage and Administration (2.2), Warnings and Precautions (5.2, 5.4), Overdosage (10)].

5.4 Risks from Concomitant Use with Benzodiazepines or Other CNS Depressants

Profound sedation, respiratory depression, coma, and death may result from the concomitant use of Oxycodone Hydrochloride Oral Solution with benzodiazepines and/or other CNS depressants, including alcohol (e.g., non-benzodiazepine sedatives/hypnotics, anxiolytics, tranquilizers, muscle relaxants, general anesthetics, antipsychotics, other opioids). Because of these risks, reserve concomitant prescribing of these drugs for use in patients for whom alternative treatment options are inadequate.

Observational studies have demonstrated that concomitant use of opioid analgesics and benzodiazepines increases the risk of drug-related mortality compared to use of opioid analgesics alone. Because of similar pharmacological properties, it is reasonable to expect similar risk with the concomitant use of other CNS depressant drugs with opioid analgesics [see Drug Interactions (7)].

If the decision is made to prescribe a benzodiazepine or other CNS depressant concomitantly with an opioid analgesic, prescribe the lowest effective dosages and minimum durations of concomitant use. In patients already receiving an opioid analgesic, prescribe a lower initial dose of the benzodiazepine or other CNS depressant than indicated in the absence of an opioid, and titrate based on clinical response. If an opioid analgesic is initiated in a patient already taking a benzodiazepine or other CNS depressant, prescribe a lower initial dose of the opioid analgesic, and titrate based on clinical response. Inform patients and caregivers of this potential interaction and educate them on the signs and symptoms of respiratory depression (including sedation).

If concomitant use is warranted, consider prescribing naloxone for the emergency treatment of opioid overdose [see Dosage and Administration (2.2), Warnings and Precautions (5.3), Overdosage (10)].

Advise both patients and caregivers about the risks of respiratory depression and sedation when Oxycodone Hydrochloride Oral Solution is used with benzodiazepines or other CNS depressants (including alcohol and illicit drugs). Advise patients not to drive or operate heavy machinery until the effects of concomitant use of the benzodiazepine or other CNS depressant have been determined. Screen patients for risk of substance use disorders, including opioid abuse and misuse, and warn them of the risk for overdose and death associated with the use of additional CNS depressants including alcohol and illicit drugs [see Drug Interactions (7)].

5.5 Neonatal Opioid Withdrawal Syndrome

Use of Oxycodone Hydrochloride Oral Solution for an extended period of time during pregnancy can result in withdrawal in the neonate. Neonatal opioid withdrawal syndrome, unlike opioid withdrawal syndrome in adults, may be life-threatening if not recognized and treated, and requires management according to protocols developed by neonatology experts. Observe newborns for signs of neonatal opioid withdrawal syndrome and manage accordingly. Advise pregnant women using opioids for an extended period of time of the risk of neonatal opioid withdrawal syndrome and ensure that appropriate treatment will be available [see Use in Specific Populations (8.1)].

5.6 Opioid Analgesic Risk Evaluation and Mitigation Strategy (REMS)

To ensure that the benefits of opioid analgesics outweigh the risks of addiction, abuse, and misuse, the Food and Drug Administration (FDA) has required a Risk Evaluation and Mitigation Strategy (REMS) for these products. Under the requirements of the REMS, drug companies with approved opioid analgesic products must make REMS-compliant education programs available to healthcare providers. Healthcare providers are strongly encouraged to do all of the following:

- Complete a REMS compliant education programoffered by an accredited provider of continuing education (CE) or another education program that includes all the elements of the FDA Education Blueprint for Health Care Providers Involved in the Management or Support of Patients with Pain.
- Discuss the safe use, serious risks, and proper storage and disposal of opioid analgesics with patients and/or their caregivers every time these medicines are prescribed. The Patient Counseling Guide (PCG) can be obtained at this link: www.fda.gov/OpioidAnalgesicREMSPCG.
- Emphasize to patients and their caregivers the importance of reading the Medication Guide that they will receive from their pharmacist every time an opioid analgesic is dispensed to them.
- Consider using other tools to improve patient, household, and community safety, such as patient-prescriber agreements that reinforce patient prescriber responsibilities.

To obtain further information on the opioid analgesic REMS and for a list of accredited REMS CME/CE, call 1-800-503-0784, or log on to www.opioidanalgesicrems.com. The FDA Blueprint can be found at www.fda/gov/OpioidAnalgesicREMSBlueprint.

5.7 Risks of Concomitant Use or Discontinuation of Cytochrome P450 3A4 Inhibitors and Inducers

Concomitant use of Oxycodone Hydrochloride Oral Solution with a CYP3A4 inhibitor, such as macrolide antibiotics (e.g., erythromycin), azole-antifungal agents (e.g., ketoconazole), and protease inhibitors (e.g., ritonavir), may increase plasma concentrations of oxycodone and prolong opioid adverse reactions, which may cause potentially fatal respiratory depression [see Warnings and Precautions (5.3)], particularly when an inhibitor is added after a stable dose of Oxycodone Hydrochloride Oral Solution is achieved. Similarly, discontinuation of a CYP3A4 inducer, such as rifampin, carbamazepine, and phenytoin, in Oxycodone Hydrochloride Oral Solution-treated patients may increase oxycodone plasma concentrations and prolong opioid adverse reactions. When using Oxycodone Hydrochloride Oral Solution with CYP3A4 inhibitors or discontinuing CYP3A4 inducers in Oxycodone Hydrochloride Oral Solution-treated patients, evaluate patients at frequent intervals and consider dosage reduction of Oxycodone Hydrochloride Oral Solution until stable drug effects are achieved [see Dosage and Administration (2.1), Drug Interactions (7)].

Concomitant use of Oxycodone Hydrochloride Oral Solution with CYP3A4 inducers or discontinuation of an CYP3A4 inhibitor could decrease oxycodone plasma concentrations, decrease opioid efficacy or, possibly, lead to a withdrawal syndrome in a patient who had developed physical dependence to oxycodone. When using Oxycodone Hydrochloride Oral Solution with CYP3A4 inducers or discontinuing CYP3A4 inhibitors, evaluate patients at frequent intervals and consider increasing the opioid dosage if needed to maintain adequate analgesia or if symptoms of opioid withdrawal occur [see Dosage and Administration (2.1), Drug Interactions (7)].

5.8 Opioid-Induced Hyperalgesia and Allodynia

Opioid-Induced Hyperalgesia (OIH) occurs when an opioid analgesic paradoxically causes an increase in pain, or an increase in sensitivity to pain. This condition differs from tolerance, which is the need for increasing doses of opioids to maintain a defined effect [see Dependence (9.3)]. Symptoms of OIH include (but may not be limited to) increased levels of pain upon opioid dosage increase, decreased levels of pain upon opioid dosage decrease, or pain from ordinarily non-painful stimuli (allodynia). These symptoms may suggest OIH only if there is no evidence of underlying disease progression, opioid tolerance, opioid withdrawal, or addictive behavior.

Cases of OIH have been reported, both with short-term and longer-term use of opioid analgesics. Though the mechanism of OIH is not fully understood, multiple biochemical pathways have been implicated. Medical literature suggests a strong biologic plausibility between opioid analgesics and OIH and allodynia. If a patient is suspected to be experiencing OIH, carefully consider appropriately decreasing the dose of the current opioid analgesic or opioid rotation (safely switching the patient to a different opioid moiety) [see Dosage and Administration (2.5), Warnings and Precautions (5.15)].

5.9 Life-Threatening Respiratory Depression in Patients with Chronic Pulmonary Disease or in Elderly, Cachectic, or Debilitated Patients

The use of Oxycodone Hydrochloride Oral Solution in patients with acute or severe bronchial asthma in an unmonitored setting or in the absence of resuscitative equipment is contraindicated.

Patients with Chronic Pulmonary Disease: Oxycodone Hydrochloride Oral Solution-treated patients with significant chronic obstructive pulmonary disease or cor pulmonale, and those with a substantially decreased respiratory reserve, hypoxia, hypercapnia, or pre-existing respiratory depression are at increased risk of decreased respiratory drive including apnea, even at recommended dosages of Oxycodone Hydrochloride Oral Solution [see Warnings and Precautions (5.3)].

Elderly, Cachectic, or Debilitated Patients:Life-threatening respiratory depression is more likely to occur in elderly, cachectic, or debilitated patients because they may have altered pharmacokinetics or altered clearance compared to younger, healthier patients [see Warnings and Precautions (5.3)].

Regularly evaluate patients, particularly when initiating and titrating Oxycodone Hydrochloride Oral Solution and when Oxycodone Hydrochloride Oral Solution is given concomitantly with other drugs that depress respiration [see Warnings and Precautions (5.3, 5.4), Drug Interactions (7)] . Alternatively, consider the use of non-opioid analgesics in these patients.

5.10 Adrenal Insufficiency

Cases of adrenal insufficiency have been reported with opioid use, more often following greater than one month of use. Presentation of adrenal insufficiency may include non-specific symptoms and signs including nausea, vomiting, anorexia, fatigue, weakness, dizziness, and low blood pressure. If adrenal insufficiency is suspected, confirm the diagnosis with diagnostic testing as soon as possible. If adrenal insufficiency is diagnosed, treat with physiologic replacement doses of corticosteroids. Wean the patient off of the opioid to allow adrenal function to recover and continue corticosteroid treatment until adrenal function recovers.

Other opioids may be tried as some cases reported use of a different opioid without recurrence of adrenal insufficiency. The information available does not identify any particular opioids as being more likely to be associated with adrenal insufficiency.

5.11 Severe Hypotension

Oxycodone Hydrochloride Oral Solution may cause severe hypotension including orthostatic hypotension and syncope in ambulatory patients. There is increased risk in patients whose ability to maintain blood pressure has already been compromised by a reduced blood volume or concurrent administration of certain CNS depressant drugs e.g., phenothiazines or general anesthetics) [see Drug Interactions (7)]. Regularly evaluate these patients for signs of hypotension after initiating or titrating the dosage of Oxycodone Hydrochloride Oral Solution. In patients with circulatory shock, Oxycodone Hydrochloride Oral Solution may cause vasodilation that can further reduce cardiac output and blood pressure. Avoid the use of Oxycodone Hydrochloride Oral Solution in patients with circulatory shock.

5.12 Risks of Use in Patients with Increased Intracranial Pressure, Brain Tumors, Head Injury, or Impaired Consciousness

In patients who may be susceptible to the intracranial effects of C02retention (e.g., those with evidence of increased intracranial pressure or brain tumors), Oxycodone Hydrochloride Oral Solution may reduce respiratory drive, and the resultant C02 retention can further increase intracranial pressure. Monitor such patients for signs of sedation and respiratory depression, particularly when initiating therapy with Oxycodone Hydrochloride Oral Solution.

Opioids may also obscure the clinical course in a patient with a head injury. Avoid the use of Oxycodone Hydrochloride Oral Solution in patients with impaired consciousness or coma.

5.13 Risks of Use in Patients with Gastrointestinal Conditions

Oxycodone Hydrochloride Oral Solution is contraindicated in patients with known or suspected gastrointestinal obstruction, including paralytic ileus.

The oxycodone in Oxycodone Hydrochloride Oral Solution may cause spasm of the sphincter of Oddi. Opioids may cause increases in serum amylase. Regularly evaluate patients with biliary tract disease, including acute pancreatitis for worsening symptoms.

5.14 Increased Risk of Seizures in Patients with Seizure Disorders

The oxycodone in Oxycodone Hydrochloride Oral Solution may increase the frequency of seizures in patients with seizure disorders and may increase the risk of seizures occurring in other clinical settings associated with seizures. regularly evaluate patients with a history of seizure disorders for worsened seizure control during Oxycodone Hydrochloride Oral Solution therapy.

5.15 Withdrawal

Do not abruptly discontinue Oxycodone Hydrochloride Oral Solution in a patient physically dependent on opioids. When discontinuing Oxycodone Hydrochloride Oral Solution in a physically-dependent patient, gradually taper the dosage. Rapid tapering of oxycodone in a patient physically dependent on opioids may lead to a withdrawal syndrome and return of pain [see Dosage and Administration (2.5), Drug Abuse and Dependence (9.3)].

Additionally, avoid the use of mixed agonist/antagonist (e.g., pentazocine, nalbuphine, and butorphanol) analgesics in patients who are receiving full opioid agonist analgesic, including Oxycodone Hydrochloride Oral Solution. In these patients, mixed agonist/antagonist and partial agonist analgesics may reduce the analgesic effect and/or precipitate withdrawal symptoms [see Drug Interactions (7)].

5.16 Risks of Driving and Operating Machinery

Oxycodone Hydrochloride Oral Solution may impair the mental or physical abilities needed to perform potentially hazardous activities such as driving a car or operating machinery. Warn patients not to drive or operate dangerous machinery unless they are tolerant to the effects of Oxycodone Hydrochloride Oral Solution and know how they will react to the medication.

6 ADVERSE REACTIONS

The following serious adverse reactions are described, or described in greater detail, in other sections:

- Addiction, Abuse, and Misuse [see Warnings and Precautions (5.2)]
- Life-Threatening Respiratory Depression [see Warnings and Precautions (5.3)]
- Interactions with Benzodiazepines or Other CNS Depressants [see Warnings and Precautions (5.4)]
- Neonatal Opioid Withdrawal Syndrome [see Warnings and Precautions (5.5)]
- Opioid-Induced Hyperalgesia and Allodynia [see Warnings and Precautions (5.8)]
- Adrenal Insufficiency [see Warnings and Precautions (5.10)]
- Severe Hypotension [ see Warnings and Precautions (5.11)]
- Gastrointestinal Adverse Reactions [see Warnings and Precautions (5.13)]
- Seizures [see Warnings and Precautions (5.14)]
- Withdrawal [see Warnings and Precautions (5.15)]

The following adverse reactions associated with the use of oxycodone were identified in clinical studies or postmarketing reports. Because some of these reactions were reported voluntarily from a population of uncertain size, it is not always possible to reliably estimate their frequency or establish a causal relationship to drug exposure.

Serious adverse reactions associated with oxycodone use included: respiratory depression, respiratory arrest, circulatory depression, cardiac arrest, hypotension, and/or shock.

The common adverse reactions seen on initiation of therapy with oxycodone are dose-related and are typical opioid-related adverse reactions. The most frequent adverse events include nausea, constipation, vomiting, headache, and pruritus. The frequency of these reactions depended on several factors, including clinical setting, the patient's level of opioid tolerance, and host factors specific to the individual.

In all patients for whom dosing information was available (n=191) from the open-label and double-blind studies involving another formulation of immediate-release oxycodone, the following adverse events were recorded in oxycodone treated patients with an incidence ≥ 3%. In descending order of frequency, they were: nausea, constipation, vomiting, headache, pruritus, insomnia, dizziness, asthenia, and somnolence.

The other less frequently observed adverse reactions from opioid analgesics, including Oxycodone Hydrochloride Oral Solution included:

Body as a Whole:abdominal pain, accidental injury, allergic reaction, back pain, chills and fever, fever, flu syndrome, infection, neck pain, pain, photosensitivity reaction, and sepsis.

Cardiovascular:deep thrombophlebitis, heart failure, hemorrhage, hypotension, migraine, palpitation, and tachycardia.

Digestive:anorexia, diarrhea, dyspepsia, dysphagia, gingivitis, glossitis, and nausea and vomiting.

Hemic and Lymphatic:anemia and leukopenia.

Metabolic and Nutritional:edema, gout, hyperglycemia, iron deficiency anemia and peripheral edema.

Musculoskeletal:arthralgia, arthritis, bone pain, myalgia and pathological fracture.

Nervous:agitation, anxiety, confusion, dry mouth, hypertonia, hypesthesia, nervousness, neuralgia, personality disorder, tremor, and vasodilation.

Respiratory:bronchitis, cough increased, dyspnea, epistaxis, laryngismus, lung disorder, pharyngitis, rhinitis, and sinusitis.

Skin and Appendages:herpes simplex, rash, sweating, and urticaria.

Special Senses:amblyopia.

Urogenital: urinary tract infection

Serotonin syndrome:Cases of serotonin syndrome, a potentially life threatening condition, have been reported during concomitant use of opioids with serotonergic drugs.

Adrenal insufficiency:Cases of adrenal insufficiency have been reported with opioid use, more often following greater than one month of use.

Anaphylaxis:Anaphylaxis has been reported with ingredients contained in Oxycodone Hydrochloride Oral Solution.

Androgen deficiency:Cases of androgen deficiency have occurred with use of opioids for an extended period of time [see Clinical Pharmacology (12.2)].

Hyperalgesia and Allodynia:Cases of hyperalgesia and allodynia have been reported with opioid therapy of any duration [see Warnings and Precautions (5.8)].

Hypoglycemia:Cases of hypoglycemia have been reported in patients taking opioids. Most reports were in patients with at least one predisposing risk factor (e.g., diabetes).

7 DRUG INTERACTIONS

Table 1 includes clinically significant drug interactions with Oxycodone Hydrochloride Oral Solution.

Table 1: Clinically Significant Drug Interactions with Oxycodone Hydrochloride Oral Solution
Inhibitors of CYP3A4 and CYP2D6
Clinical Impact: | The concomitant use of Oxycodone Hydrochloride Oral Solution and CYP3A4 inhibitors can increase the plasma concentration of oxycodone, resulting in increased or prolonged opioid effects. These effects could be more pronounced with concomitant use of Oxycodone Hydrochloride Oral Solution and CYP2D6 and CYP3A4 inhibitors, particularly when an inhibitor is added after a stable dose of Oxycodone Hydrochloride Oral Solution is achieved [see Warnings and Precautions (5.7)]. After stopping a CYP3A4 inhibitor, as the effects of the inhibitor decline, the oxycodone plasma concentration will decrease [see Clinical Pharmacology (12.3)] , resulting in decreased opioid efficacy or a withdrawal syndrome in patients who had developed physical dependence to oxycodone.
Intervention: | If concomitant use is necessary, consider dosage reduction of Oxycodone Hydrochloride Oral Solution until stable drug effects are achieved. Evaluate patients at frequent intervals for respiratory depression and sedation. If a CYP3A4 inhibitor is discontinued, consider increasing the Oxycodone Hydrochloride Oral Solution dosage until stable drug effects are achieved. Evaluate for signs of opioid withdrawal.
Examples: | Macrolide antibiotics (e.g., erythromycin, azole-antifungal agents (e.g., ketoconazole), protease inhibitors (e.g., ritonavir)
CYP3A4 Inducers
Clinical Impact: | The concomitant use of Oxycodone Hydrochloride Oral Solution and CYP3A4 inducers can decrease the plasma concentration of oxycodone [see Clinical Pharmacology (12.3)], resulting in decreased efficacy or onset of a withdrawal syndrome in patients who have developed physical dependence to oxycodone [see Warnings and Precautions (5.15)] . After stopping a CYP3A4 inducer, as the effects of the inducer decline, the oxycodone plasma concentration will increase [see Clinical Pharmacology (12.3)] , which could increase or prolong both the therapeutic effects and adverse reactions and may cause serious respiratory depression.
Intervention: | If concomitant use is necessary, consider increasing the Oxycodone Hydrochloride Oral Solution dosage until stable drug effects are achieved. Evaluate patients for signs of opioid withdrawal and sedation. If a CYP3A4 inducer is discontinued, consider Oxycodone Hydrochloride Oral Solution dosage reduction and evaluate patients at frequent intervals for signs of respiratory depression and sedation.
Examples | Rifampin, carbamazepine, phenytoin
Benzodiazepines and other Central Nervous System (CNS) Depressants
Clinical Impact: | Due to additive pharmacologic effect, the concomitant use of benzodiazepines or other CNS depressants, including alcohol, can increase the risk of hypotension, respiratory depression, profound sedation, coma, and death.
Intervention: | Reserve concomitant prescribing of these drugs for use in patients for whom alternative treatment options are inadequate. Limit dosages and durations to the minimum required. Inform patients and caregivers of this potential interaction and educate them on the signs and symptoms of respiratory depression (including sedation). If concomitant use is warranted, consider prescribing naloxone for the emergency treatment of opioid overdose [see Dosage and Administration (2.2), Warnings and Precautions (5.2, 5.3, 5.4)] .
Examples: | Benzodiazepines and other sedatives/hypnotics, anxiolytics, tranquilizers, muscle relaxants, general anesthetics, antipsychotics, other opioids, alcohol.
Serotonergic Drugs
Clinical Impact: | The concomitant use of opioids with other drugs that affect the serotonergic neurotransmitter system has resulted in serotonin syndrome.
Intervention: | If concomitant use is warranted, frequently reevaluate the patient, particularly during treatment initiation and dose adjustment. Discontinue Oxycodone Hydrochloride Oral Solution if serotonin syndrome is suspected.
Examples: | Selective serotonin reuptake inhibitors (SSRIs), serotonin and norepinephrine reuptake inhibitors (SNRIs), tricyclic antidepressants (TCAs), triptans, 5-HT3 receptor antagonists, drugs that affect the serotonin neurotransmitter system (e.g., mirtazapine, trazodone, tramadol), certain muscle relaxants (i.e., cyclobenzaprine, metaxalone), monoamine oxidase (MAO) inhibitors (those intended to treat psychiatric disorders and also others, such as linezolid and intravenous methylene blue).
Monoamine Oxidase Inhibitors (MAOIs)
Clinical Impact: | MAOI interactions with opioids may manifest as serotonin syndrome or opioid toxicity (e.g., respiratory depression, coma) [see Warnings and Precautions (5.3)] .
Intervention: | The use of Oxycodone Hydrochloride Oral Solution is not recommended for patients taking MAOIs or within 14 days of stopping such treatment. If urgent use of an opioid is necessary, use test doses and frequent titration of small doses to treat pain while closely monitoring blood pressure and signs and symptoms of CNS and respiratory depression.
Examples: | phenelzine, tranylcypromine, linezolid
Mixed Agonist/Antagonist and Partial Agonist Opioid Analgesics
Clinical Impact: | May reduce the analgesic effect of Oxycodone Hydrochloride Oral Solution and/or precipitate withdrawal symptoms.
Intervention: | Avoid concomitant use.
Examples: | butorphanol, nalbuphine, pentazocine, buprenorphine
Muscle Relaxants
Clinical Impact: | Oxycodone may enhance the neuromuscular blocking action of skeletal muscle relaxants and produce an increased degree of respiratory depression.
Intervention: | Because respiratory depression that may be greater than otherwise expected, decrease the dosage of Oxycodone Hydrochloride Oral Solution and/or the muscle relaxant as necessary. Due to the risk of respiratory depression with concomitant use of skeletal muscle relaxants and opioids, consider prescribing naloxone for the emergency treatment of opioid overdose [see Dosage and Administration (2.2, Warnings and Precautions (5.3, 5.4)] .
Diuretics
Clinical Impact: | Opioids can reduce the efficacy of diuretics by inducing the release of antidiuretic antidiuretic hormone.
Intervention: | Evaluate patients for signs of diminished diuresis and/or effects on blood pressure and increase the dosage of the diuretic as needed.
Anticholinergic Drugs
Clinical Impact: | The concomitant use of anticholinergic drugs may increase risk of urinary retention and/or severe constipation, which may lead to paralytic ileus.
Intervention: | Evaluate patients for signs of urinary retention or reduced gastric motility when Oxycodone Hydrochloride Oral Solution is used concomitantly with anticholinergic drugs.

8 USE IN SPECIFIC POPULATIONS

8.1 Pregnancy

Risk Summary

Use of opioid analgesics for an extended period of time during pregnancy may cause neonatal opioid withdrawal syndrome [see Warnings and Precautions (5.5)] . Available data with Oxycodone Hydrochloride Oral Solution are insufficient to inform a drug-associated risk for major birth defects and miscarriage.

Animal reproduction studies with oral administrations of oxycodone hydrochloride in rats and rabbits during the period of organogenesis at doses 2.6 and 8.1 times, respectively, the human dose of 60 mg/day did not reveal evidence of teratogenicity or embryo-fetal toxicity. In several published studies, treatment of pregnant rats with oxycodone at clinically relevant doses and below, resulted in neurobehavioral effects in offspring [see Data]. Based on animal data, advise pregnant women of the potential risk to a fetus.

The background risk of major birth defects and miscarriage for the indicated population is unknown. All pregnancies have a background risk of birth defect, loss, or other adverse outcomes. In the U.S. general population, the estimated background risk of major birth defects and miscarriage in clinically recognized pregnancies is 2 to 4% and 15 to 20%, respectively.

Clinical Considerations

Fetal/Neonatal Adverse Reactions

Use of opioid analgesics for an extended period of time during pregnancy for medical or nonmedical purposes can result in physical dependence in the neonate and neonatal opioid withdrawal syndrome shortly after birth.

Neonatal opioid withdrawal syndrome presents as irritability, hyperactivity and abnormal sleep pattern, high pitched cry, tremor, vomiting, diarrhea, and failure to gain weight. The onset, duration, and severity of neonatal opioid withdrawal syndrome vary based on the specific opioid used, duration of use, timing and amount of last maternal use, and rate of elimination of the drug by the newborn. Observe newborns for symptoms of neonatal opioid withdrawal syndrome and manage accordingly [see Warnings and Precautions (5.5)].

Labor or Delivery

Opioids cross the placenta and may produce respiratory depression and psycho-physiologic effects in neonates. An opioid antagonist, such as naloxone, must be available for reversal of opioid-induced respiratory depression in the neonate. Oxycodone Hydrochloride Oral Solution is not recommended for use in pregnant women during or immediately prior to labor, when other analgesic techniques are more appropriate. Opioid analgesics, including Oxycodone Hydrochloride Oral Solution, can prolong labor through actions which temporarily reduce the strength, duration, and frequency of uterine contractions. However, this effect is not consistent and may be offset by an increased rate of cervical dilation, which tends to shorten labor. Monitor neonates exposed to opioid analgesics during labor for signs of excess sedation and respiratory depression.

Data

Animal Data

In embryo-fetal development studies in rats and rabbits, pregnant animals received oral doses of oxycodone hydrochloride administered during the period of organogenesis up to 16 mg/kg/day and up 25 mg/kg/day, respectively. These studies revealed no evidence of teratogenicity or embryo-fetal toxicity due to oxycodone. The highest doses tested in rats and rabbits were equivalent to approximately 2.6 and 8.1 times an adult human dose of 60 mg/day, respectively, on a mg/m^2basis. In published studies, offspring of pregnant rats administered oxycodone during gestation have been reported to exhibit neurobehavioral effects including altered stress responses, increased anxiety-like behavior (2 mg/kg/day IV from Gestation Day 8 to 21 and Postnatal Day 1, 3, and 5; 0.3 times an adult human dose of 60 mg/day, on a mg/m2 basis) and altered learning and memory (15 mg/kg/day orally from breeding through parturition; 2.4 times an adult human dose of 60 mg/day, on a mg/m^2basis).

8.2 Lactation

Risk Summary

Available data from lactation studies indicate that oxycodone is present in breastmilk and that doses of less than 60 mg/day of the immediate-release formulation are unlikely to result in clinically relevant exposures in breastfed infants. A pharmacokinetics study utilizing opportunistic sampling of 76 lactating women receiving oxycodone immediate-release products for postpartum pain management showed that oxycodone concentrates in breastmilk with an average milk to plasma ratio of 3.2. The relative infant dose was low, approximately 1.3% of a weight-adjusted maternal dose (see Data) .

In the same study, among the 70 infants exposed to oxycodone in breastmilk, no adverse events were attributed to oxycodone. However, based on known adverse effects in adults, infants should be monitored for signs of excess sedation and respiratory depression (see Clinical Considerations) . There are no data on the effects of the oxycodone on milk production.

The developmental and health benefits of breastfeeding should be considered along with the mother's clinical need for Oxycodone Hydrochloride Oral Solution and any potential adverse effects on the breastfed infant from Oxycodone Hydrochloride Oral Solution or from the underlying maternal condition.

Clinical Considerations

Monitor infants exposed to Oxycodone Hydrochloride Oral Solution through breast milk for excess sedation and respiratory depression. Withdrawal symptoms can occur in breastfed infants when maternal administration of an opioid analgesic is stopped, or when breastfeeding is stopped.

Data

Oxycodone concentration data from 76 lactating women receiving immediate-release oxycodone products for postpartum pain management, and 28 infants exposed to oxycodone in breastmilk showed that following a median (range) dose of oxycodone in mothers of 9.2 (5-10) mg/dose or 33.0 (5.4-59.3) mg/day, oxycodone concentrated in breastmilk with a median (range) milk to plasma ratio of 3.2 (1.2-5.3). However, when using maternal breastmilk data to estimate the daily and relative infant dose, the infant dose was 0.006 mg/kg/day, which is 1.3% of a weight-adjusted maternal dose of 10 mg every 6 hours. These estimates based on maternal breastmilk concentrations were corroborated by the observed infant concentrations, of which over 75% (19/25) were below the limit of quantification. Among the 6 infants with quantifiable concentration, the median (range) concentration was 0.2 ng/mL (0.1-0.7). These concentrations are 100 to 1000 times lower than concentrations observed in other studies after infants received oxycodone at 0.1 mg/kg/dose (~20-200 ng/mL).

8.3 Females and Males of Reproductive Potential

Infertility

Use of opioids for an extended period of time may cause reduced fertility in females and males of reproductive potential. It is not known whether these effects on fertility are reversible [see Adverse Reactions (6), Clinical Pharmacology (12.2)].

8.4 Pediatric Use

The safety and effectiveness of Oxycodone Hydrochloride Oral Solution have not been established in pediatric patients.

The safety and pharmacokinetics of a single-dose of an Oxycodone Hydrochloride Oral Solution were evaluated in an open-label clinical trial in 89 pediatric patients 2 years to less than 17 years of age with postoperative pain. However definitive conclusions were not possible because of insufficient information.

8.5 Geriatric Use

Elderly patients (aged 65 years or older) may have increased sensitivity to oxycodone. In general, use caution when selecting a dose for an elderly patient, usually starting at the low end of the dosing range, reflecting the greater frequency of decreased hepatic, renal, or cardiac function and of concomitant disease or other drug therapy.

Respiratory depression is the chief risk for elderly patients treated with opioids and has occurred after large initial doses were administered to patients who were not opioid-tolerant or when opioids were co-administered with other agents that depress respiration. Titrate the dosage of Oxycodone Hydrochloride Oral Solution slowly in geriatric patients and frequently reevaluate the patient for signs of central nervous system and respiratory depression [see Warnings and Precautions (5.9)].

Oxycodone is known to be substantially excreted by the kidney, and the risk of adverse reactions to this drug may be greater in patients with impaired renal function. Because elderly patients are more likely to have decreased renal function, care should be taken in dose selection, and it may be useful to regularly evaluate renal function.

8.6 Hepatic Impairment

Since oxycodone is extensively metabolized in the liver, its clearance may decrease in patients with hepatic impairment. Initiate therapy in these patients with a lower than usual dosage of Oxycodone Hydrochloride Oral Solution and titrate carefully. Regularly evaluate for adverse events such as respiratory depression, sedation, and hypotension [see Clinical Pharmacology (12.3)].

8.7 Renal Impairment

Information from oxycodone tablets indicate that patients with renal impairment had higher plasma concentrations of oxycodone than subjects with normal renal function. Initiate therapy with a lower than usual dosage of Oxycodone Hydrochloride Oral Solution and titrate carefully. Regularly evaluate for adverse events such as respiratory depression, sedation, and hypotension [see Clinical Pharmacology (12.3)].

9 DRUG ABUSE AND DEPENDENCE

9.1 Controlled Substance

Oxycodone Hydrochloride Oral Solution contains oxycodone, a Schedule II controlled substance.

9.2 Abuse

Oxycodone Hydrochloride Oral Solution contains oxycodone, a substance with high potential for misuse and abuse, which can lead to the development of substance use disorder, including addiction [see Warnings and Precautions (5.2)].

Misuse is the intentional use, for therapeutic purposes, of a drug by an individual in a way other than prescribed by a healthcare provider or for whom it was not prescribed.

Abuse is the intentional, non-therapeutic use of a drug, even once, for its desirable psychological or physiological effects.

Drug addiction is a cluster of behavioral, cognitive, and physiological phenomena that may include a strong desire to take the drug, difficulties in controlling drug use (e.g., continuing drug use despite harmful consequences, giving a higher priority to drug use than other activities and obligations), and possible tolerance or physical dependence.

Misuse and abuse of Oxycodone Hydrochloride Oral Solution increases risk of overdose, which may lead to central nervous system and respiratory depression, hypotension, seizures, and death. The risk is increased with concurrent abuse of Oxycodone Hydrochloride Oral Solution with alcohol and/or other CNS depressants. Abuse of and addiction to opioids in some individuals may not be accompanied by concurrent tolerance and symptoms of physical dependence. In addition, abuse of opioids can occur in the absence of addiction.

All patients treated with opioids require careful and frequent reevaluation for signs of misuse, abuse, and addiction, because use of opioid analgesic products carries the risk of addiction even under appropriate medical use. Patients at high risk of Oxycodone Hydrochloride Oral Solution abuse include those with a history of prolonged use of any opioid, including products containing oxycodone, those with a history of drug or alcohol abuse, or those who use Oxycodone Hydrochloride Oral Solution in combination with other abused drugs.

"Drug-seeking" behavior is very common in persons with substance use disorders. Drug-seeking tactics include emergency calls or visits near the end of office hours, refusal to undergo appropriate examination, testing, or referral, repeated "loss" of prescriptions, tampering with prescriptions, and reluctance to provide prior medical records or contact information for other treating healthcare provider(s). "Doctor shopping" (visiting multiple prescribers to obtain additional prescriptions) is common among people who abuse drugs and people with substance use disorder. Preoccupation with achieving adequate pain relief can be appropriate behavior in a patient with inadequate pain control.

Oxycodone Hydrochloride Oral Solution, like other opioids, can be diverted for nonmedical use into illicit channels of distribution. Careful record-keeping of prescribing information, including quantity, frequency, and renewal requests, as required by state and federal law, is strongly advised.

Proper assessment of the patient, proper prescribing practices, periodic reevaluation of therapy, and proper dispensing and storage are appropriate measures that help to limit abuse of opioid drugs.

Risks Specific to Abuse of Oxycodone Hydrochloride Oral Solution

Abuse of Oxycodone Hydrochloride oral Solution poses a risk of overdose and death. The risk is increased with concurrent use of Oxycodone Hydrochloride Oral Solution with alcohol and/or other CNS depressants.

Oxycodone Hydrochloride Oral Solution is approved for oral use only.

Parenteral drug abuse is commonly associated with transmission of infectious diseases such as hepatitis and HIV.

9.3 Dependence

Both tolerance and physical dependence can develop during use of opioid therapy.

Tolerance is a physiological state characterized by a reduced response to a drug after repeated administration (i.e., a higher dose of a drug is required to produce the same effect that was once obtained at a lower dose).

Physical dependence is a state that develops as a result of a physiological adaptation in response to repeated drug use, manifested by withdrawal signs and symptoms after abrupt discontinuation or a significant dose reduction of a drug.

Withdrawal may be precipitated through the administration of drugs with opioid antagonist activity (e.g., naloxone), missed agonist/antagonist analgesics (e.g., pentazocine, butorphanol, nalbuphine), or partial agonists (e.g., buprenorphine). Physical dependence may not occur to a clinically significant degree until after several days to weeks of continued use.

Do not abruptly discontinue Oxycodone Hydrochloride Oral Solution in a patient physically dependent on opioids. Rapid tapering of Oxycodone Hydrochloride Oral Solution in a patient physically dependent on opioids may lead to serious withdrawal symptoms, uncontrolled pain, and suicide. Rapid discontinuation has also been associated with attempts to find other sources of opioid analgesics, which may be confused with drug-seeking for abuse.

When discontinuing Oxycodone Hydrochloride Oral Solution, gradually taper the dosage using a patient-specific plan that considers the following: the dose of Oxycodone Hydrochloride Oral Solution the patient has been taking, the duration of treatment, and the physical and psychological attributes of the patient. To improve the likelihood of a successful taper and minimize withdrawal symptoms, it is important that the opioid tapering schedule is agreed upon by the patient. In patients taking opioids for an extended period of time at high doses, ensure that a multimodal approach to pain management, including mental health support (if needed), is in place prior to initiating an opioid analgesic taper [see Dosage and Administration (2.5), Warnings and Precautions (5.15)].

Infants born to mothers physically dependent on opioids will also be physically dependent and may exhibit respiratory difficulties and withdrawal signs [see Use in Specific Populations (8.1)].

10 OVERDOSAGE

Clinical Presentation

Acute overdose with oxycodone can be manifested by respiratory depression, somnolence progressing to stupor or coma, skeletal muscle flaccidity, cold and clammy skin, constricted pupils, and, in some cases, pulmonary edema, bradycardia, hypotension, hypoglycemia, partial or complete airway obstruction, atypical snoring, and death. Marked mydriasis rather than miosis may be seen with hypoxia in overdose situations [see Clinical Pharmacology (12.2)].

Treatment of Overdose

In case of overdose, priorities are the reestablishment of a patent and protected airway and institution of assisted or controlled ventilation, if needed. Employ other supportive measures (including oxygen and vasopressors) in the management of circulatory shock and pulmonary edema as indicated. Cardiac arrest or arrhythmias will require advanced life-support measures.

Opioid antagonists, such as naloxone, are specific antidotes to respiratory depression resulting from opioid overdose. For clinically significant respiratory or circulatory depression secondary to opioid overdose, administer an opioid antagonist.

Because the duration of opioid reversal is expected to be less than the duration of action of oxycodone in Oxycodone Hydrochloride Oral Solution, carefully monitor the patient until spontaneous respiration is reliably re-established. If the response to an opioid antagonist is suboptimal or only brief in nature, administer additional antagonist as directed by the product's prescribing information.

In an individual physically dependent on opioids, administration of the recommended usual dosage of the antagonist will precipitate an acute withdrawal syndrome. The severity of the withdrawal symptoms experienced will depend on the degree of physical dependence and the dose of the antagonist administered. If a decision is made to treat serious respiratory depression in the physically dependent patient, administration of the antagonist should be initiated with care and by titration with smaller than usual doses of the antagonist.

11. DESCRIPTION

Oxycodone Hydrochloride Oral Solution is an agonist, available as a red solution 5 mg/5 mL (1 mg/mL) and a yellow solution 100 mg/5 mL (20 mg/mL) for oral administration. The chemical name is (5R,9R,13S,14S)-4,5α-epoxy-14-hydroxy-3-methoxy-17-methylmorphinan-6-one hydrochloride. The molecular weight is 351.82.

Its molecular formula is C18H21NO4HCl, and it has the following chemical structure:

Oxycodone hydrochloride is a white, odorless crystalline powder derived from the opium alkaloid, thebaine. It is soluble in water and slightly soluble in alcohol.

The inactive ingredients in Oxycodone Hydrochloride Oral Solution, 5 mg per 5 mL (l mg/mL) include: citric acid anhydrous, FD&C Red #40, natural/artificial berry flavor, purified water, sodium citrate dihydrate, sodium benzoate, saccharin sodium, sorbitol.

The inactive ingredients in Oxycodone Hydrochloride Oral Solution 100 mg per 5 mL (20 mg/mL) include: citric acid anhydrous, D&C Yellow #10, natural/artificial berry flavor, purified water, sodium citrate dihydrate, sodium benzoate, saccharin sodium, sorbitol.

12 CLINICAL PHARMACOLOGY

12.1 Mechanism of Action

Oxycodone is a full opioid agonist and is relatively selective for the mu-opioid receptor, although it can bind to other opioid receptors at higher doses. The principal therapeutic action of oxycodone is analgesia. Like all full opioid agonists, there is no ceiling effect for analgesia with oxycodone. Clinically, dosage is titrated to provide adequate analgesia and may be limited by adverse reactions, including respiratory and CNS depression.

The precise mechanism of the analgesic action is unknown. However, specific CNS opioid receptors for endogenous compounds with opioid-like activity have been identified throughout the brain and spinal cord and are thought to play a role in the analgesic effects of this drug.

12.2 Pharmacodynamics

Effects of the Central Nervous System (CNS)

Oxycodone produces respiratory depression by direct action on brain stem respiratory centers. The respiratory depression involves a reduction in the responsiveness of the brain stem respiratory centers to both increases in carbon dioxide tension and electrical stimulation.

Oxycodone causes miosis, even in total darkness. Pinpoint pupils are a sign of opioid overdose but are not pathognomonic (e.g., pontine lesions of hemorrhagic or ischemic origins may produce similar findings). Marked mydriasis rather than miosis may be seen due to hypoxia in overdose situations.

Effects on the Gastrointestinal Tract and Other Smooth Muscle

Oxycodone causes a reduction in motility associated with an increase in smooth muscle tone in the antrum of the stomach and duodenum. Digestion of food in the small intestine is delayed and propulsive contractions are decreased. Propulsive peristaltic waves in the colon are decreased, while tone may be increased to the point of spasm resulting in constipation. Other opioid-induced effects may include a reduction in biliary and pancreatic secretions, spasm of sphincter of Oddi, and transient elevations in serum amylase.

Effects on the Cardiovascular System

Oxycodone produces peripheral vasodilation which may result in orthostatic hypotension or syncope. Manifestations of histamine release and/or peripheral vasodilation may include pruritus, flushing, red eyes and sweating and/or orthostatic hypotension.

Effects on the Endocrine System

Opioids inhibit the secretion of adrenocorticotropic hormone (ACTH, cortisol), and luteinizing hormone (LH) in humans [see Adverse Reactions (6)]. They also stimulate prolactin, growth hormone (GH) secretion, and pancreatic secretion of insulin and glucagon.

Use of opioids for an extended period of time may influence the hypothalamic-pituitary-gonadal axis, leading to androgen deficiency that may manifest as low libido, impotence, erectile dysfunction, amenorrhea, or infertility. The causal role of opioids in the clinical syndrome of hypogonadism is unknown because the various medical, physical, lifestyle, and psychological stressors that may influence gonadal hormone levels have not been adequately controlled for in studies conducted to date [see Adverse Reactions (6)].

Effects on the Immune System

Opioids have been shown to have a variety of effects on components of the immune system in in-vitro and Animal models. The clinical significance of these findings is unknown. Overall, the effects of opioids appear to be modestly immunosuppressive.

Concentration-Efficacy Relationships

The minimum effective analgesic concentration will vary widely among patients, especially among patients who have been previously treated with opioid agonists. The minimum effective analgesic concentration of oxycodone for any individual patient may increase over time due to an increase in pain, the development of a new pain syndrome and/or the development of analgesic tolerance [see Dosage and Administration (2.1, 2.3, 2.4)].

Concentration-Adverse Reaction Relationships

There is a relationship between increasing oxycodone plasma concentration and increasing frequency of dose-related opioid adverse reactions such as nausea, vomiting, CNS effects, and respiratory depression. In opioid-tolerant patients, the situation may be altered by the development of tolerance to opioid-related adverse reactions [see Dosage and Administration (2.1, 2.3, 2.4)].

12.3 Pharmacokinetics

The activity of oxycodone hydrochloride is primarily due to the parent drug oxycodone.

Absorption

About 60 to 87% of an oral dose reaches the systemic circulation in comparison to a parenteral dose. This high oral bioavailability (compared to other opioids) is due to lower pre-systemic and/or first-pass metabolism of oxycodone.

Food Effect

When oxycodone capsules are administered with a high-fat meal, mean AUC values are increased by 23% and peak concentrations are decreased by 14%. Food causes a delay in Tmax (1.00 to 3 hours). Similar effects of food are expected with the oral solution.

Distribution

Following intravenous administration, the volume of distribution (Vss) for oxycodone was 2.6 L/kg. Plasma protein binding of oxycodone at 37°C and a pH of 7.4 was about 45%. Oxycodone has been found in breast milk.

Elimination

Metabolism

Oxycodone hydrochloride is extensively metabolized by multiple metabolic pathways to noroxycodone, oxymorphone, and noroxymorphone, which are subsequently glucuronidated. CYP3A4 mediated N-demethylation to noroxycodone is the primary metabolic pathway of oxycodone with a less contribution from CYP2D6 mediated O-demethylation to oxymorphone. Therefore, the formation of these and related metabolites can, in theory, be affected by other drugs. The major circulating metabolite is noroxycodone with an AUC ratio of 0.6 relative to that of oxycodone. Noroxycodone is reported to be a considerably weaker analgesic than oxycodone. Oxymorphone, although possessing analgesic activity, is present in the plasma only in low concentrations. The correlation between oxymorphone concentrations and opioid effects was much less than that seen with oxycodone plasma concentrations. The analgesic activity profile of other metabolites is not known.

Excretion

Oxycodone and its metabolites are excreted primarily via the kidney. The amounts measured in the urine have been reported as follows: free oxycodone up to 19%; conjugated oxycodone up to 50%; free oxymorphone 0%; conjugated oxymorphone < 14%; both free and conjugated noroxycodone have been found in the urine but not quantified. The total plasma clearance was 0.8 L/min for adults. Apparent elimination half-life of oxycodone following the administration of oxycodone is approximately 4 hours.

Specific Populations

Age: Geriatric Population:

Information obtained from oxycodone tablets indicate that the plasma concentrations of oxycodone did not appear to be increased in patients over of the age of 65.

Hepatic Impairment:

Because oxycodone is extensively metabolized in the liver, its clearance may decrease in hepatic-impaired patients. A dose adjustment is recommended in these patients [see Use in Specific Populations (8.6)].

Renal Impairment:

Because this drug is known to be substantially excreted by the kidney, and the risk of adverse reactions to this drug may be greater in patients with impaired renal function, a dose reduction is recommended for renal impaired patients [see Use in Specific Populations (8.7)].

Drug Interaction Studies

CYP3A4 Inhibitors

CYP3A4 is the major enzyme involved in noroxycodone formation. A published study showed that the co-administration of voriconazole, a CYP3A4 inhibitor, increased oxycodone AUC and Cmax by 3.6 and 1.7 fold, respectively.

CYP3A4 Inducers

A published study showed that the co-administration of rifampin, a drug metabolizing enzyme inducer, decreased oxycodone AUC and Cmax values by 86% and 63%, respectively.

CYP2D6 Inhibitors

Oxycodone is metabolized in part to oxymorphone via the cytochrome P450 isoenzyme CYP2D6. While this pathway may be blocked by a variety of drugs (e.g., certain cardiovascular drugs and antidepressants), such blockade has not yet been shown to be of clinical significance with this agent.

13 NONCLINICAL TOXICOLOGY

13.1 Carcinogenesis, Mutagenesis, Impairment of Fertility

Carcinogenesis

Long-term studies in animals to evaluate the carcinogenic potential of oxycodone have not been conducted.

Mutagenesis

Oxycodone hydrochloride was genotoxic in an in-vitro mouse lymphoma assay in the presence of metabolic activation. There was no evidence of genotoxic potential in an in-vitro bacterial reverse mutation assay (Salmonella typhimurium and Escherichia coli) and in an assay for chromosomal aberrations (in-vivo mouse bone marrow micronucleus assay).

Impairment of Fertility

Studies in animals to evaluate the potential impact of oxycodone on fertility have not been conducted.

16 HOW SUPPLIED/STORAGE AND HANDLING

Oxycodone Hydrochloride Oral Solution 5 mg per 5 mL (1 mg/mL), is a red solution, supplied as:

NDC# 64950-354-10: Bottle of 100 mL supplied with a calibrated measuring cup

NDC# 64950-354-50: Bottle of 500 mL supplied with a calibrated measuring cup

NDC# 64950-354-05: 5 mL unit dose cup

NDC# 64950-354-45: Case contains 40 unit dose cups of 5 mL (NDC 64950-354-05), packaged in 4 trays of 10 unit dose cups each

NDC# 64950-354-55: Case contains 50 unit dose cups of 5 mL (NDC 64950-354-05), packaged in 5 trays of 10 unit dose cups each

Oxycodone Hydrochloride Oral Solution 100 mg per 5 mL (20 mg per mL), is a yellow solution, supplied as:

NDC# 64950-353-03: Bottle of 30 mL supplied with a calibrated oral syringe

NDC# 64950-353-01: Prefilled Oral Dispenser, 10 mg per 0.5 mL

NDC# 64950-353-02: Prefilled Oral Dispenser, 20 mg per mL

NDC# 64950-353-51: Case contains 50 prefilled oral dispensers of 10 mg/0.5 mL (NDC # 64950-353-01), packaged in 10 pouches of 5 prefilled oral dispensers each (NDC# 64950-353-91)

NDC# 64950-353-52: Case contains 50 prefilled oral dispensers of 20 mg/mL (NDC# 64950-353-02), packaged in 10 pouches of 5 prefilled oral dispensers each (NDC# 64950-353-92)

STORAGE AND HANDLING

Store at Controlled Room Temperature, 25°C (77°F); excursions are permitted to 15° - 30°C (59° - 86°F).

PROTECT from MOISTURE and LIGHT.

Store Oxycodone Hydrochloride Oral Solution securely and dispose of properly .

17 PATIENT COUNSELING INFORMATION

Advise the patient to read the FDA-approved patient labeling (Medication Guide).

Storage and Disposal:

Because of the risks associated with accidental ingestion, misuse, and abuse, advise patients to store Oxycodone Hydrochloride Oral Solution securely, out of sight and reach of children, and in a location not accessible by others, including visitors to the home. Inform patients that leaving Oxycodone Hydrochloride Oral Solution unsecured can pose a deadly risk to others in the home (see Warnings and Precautions (5.2, 5.3), Drug Abuse and Dependence (9.2)].

Advise patients and caregivers that when medicines are no longer needed, they should be disposed of promptly. Expired, unwanted, or unused Oxycodone Hydrochloride Oral Solution should be disposed of by flushing the unused medication down the toilet if a drug take-back option is not readily available. Inform patients that they can visit www.fda.gov/drugdisposalfor a complete list of medicines recommended for disposal by flushing, as well as additional information on disposal of unused medicines.

Medication Errors

Instruct patients and caregivers how to measure and take or administer the correct dose of Oxycodone Hydrochloride Oral Solution and to always use the enclosedgraduated measuring cup when administering Oxycodone Hydrochloride Oral Solution 5 mg per 5 mL (1 mg/mL) and to always use the enclosedgraduated oral syringe when administering Oxycodone Hydrochloride Oral Solution 100 mg per 5 mL (20 mg/mL) to correctly measure the prescribed amount of medication [see Dosage and Administration (2.1), Warnings and Precautions (5.1)].

Advise patients and caregivers that Oxycodone Hydrochloride Oral Solution, is available in two concentrations: 5 mg/5 mL and 100 mg/5 mL. Inform patients and caregivers about which concentration they have been prescribed and provide detailed instruction on how to measure and take or administer the correct dose of Oxycodone Hydrochloride Oral Solution, and to always use the enclosedmeasuring device when administering Oxycodone Hydrochloride Oral Solution, to ensure that the dose is measured and administered accurately.

If the prescribed concentration is changed, instruct patients and caregivers on how to correctly measure the new dose to avoid errors which could result in accidental overdose and death.

Addiction, Abuse, and Misuse

Inform patients that the use of Oxycodone Hydrochloride Oral Solution, even when taken as recommended, can result in addiction, abuse, and misuse, which can lead to overdose and death [see Warnings and Precautions (5.2)] . Instruct patients not to share Oxycodone Hydrochloride Oral Solution with others and to take steps to protect Oxycodone Hydrochloride Oral Solution from theft or misuse.

Life-Threatening Respiratory Depression

Inform patients of the risk of life-threatening respiratory depression, including information that the risk is greatest when starting Oxycodone Hydrochloride Oral Solution or when the dosage is increased, and that it can occur even at recommended dosages.

Educate patients and caregivers on how to recognize respiratory depression and emphasize the importance of calling 911 or getting emergency medical help right away in the event of a known or suspected overdose [see Warnings and Precautions (5.3)].

Accidental Ingestion

Inform patients that accidental ingestion, especially by children, may result in respiratory depression or death [see Warnings and Precautions (5.3)] .

Interactions with Benzodiazepines and Other CNS Depressants

Inform patients and caregivers that potentially fatal additive effects may occur if Oxycodone Hydrochloride Oral Solution is used with benzodiazepines or other CNS depressants, including alcohol, and not to use these concomitantly unless supervised by a healthcare provider [see Warnings and Precautions (5.4), Drug Interactions (7)].

Patient Access to Naloxone for the Emergency Treatment of Opioid Overdose

Discuss with the patient and caregiver the availability of naloxone for the emergency treatment of opioid overdose, both when initiating and renewing treatment with Oxycodone Hydrochloride Oral Solution. Inform patients and caregivers about the various ways to obtain naloxone as permitted by individual state naloxone dispensing and prescribing requirements or guidelines (e.g., by prescription, directly from a pharmacist, or as part of a community-based program) [see Dosage and Administrations (2.2), Warnings and Precautions (5.3)].

Educate patients and caregivers on how to recognize the signs and symptoms of an overdose.

Explain to patients and patients and caregivers that naloxone's effects are temporary, and that they must call 911 or get emergency medical help right away in all cases of known or suspected opioid overdose, even if naloxone is administered [see Overdosage (10)].

If naloxone is prescribed, also advise patients and caregivers:

- How to treat with naloxone in the event of an opioid overdose
- To tell family and friends about their naloxone and to keep it in a place where family and friends can access it in an emergency
- To read the Patient Information (or other educational material) that will come with their naloxone. Emphasize the importance of doing this before an opioid emergency happens, so the patient and caregiver will know what to do.

Hyperalgesia and Allodynia

Inform patients and caregivers not to increase opioid dosage without first consulting a clinician. Advise patients to seek medical attention if they experience symptoms of hyperalgesia, including worsening pain, increased sensitivity to pain, or new pain [see Warnings and Precautions (5.8), Adverse Reactions (6)].

Serotonin Syndrome

Inform patients that opioids could cause a rare but potentially life-threatening condition called serotonin syndrome resulting from concomitant administration of serotonergic drugs. Warn patients of the symptoms of serotonin syndrome and to seek medical attention right away if symptoms develop. Instruct patients to inform their healthcare providers if they are taking, or plan to take serotonergic medications. [see Drug Interactions (7)] .

MAOI Interaction

Inform patients to avoid taking Oxycodone Hydrochloride Oral Solution while using any drugs that inhibit monoamine oxidase. Patients should not start MAOIs while taking Oxycodone Hydrochloride Oral Solution [see Drug Interactions (7)].

Important Administration Instructions

Instruct patients how to properly take Oxycodone Hydrochloride Oral Solution [see Dosage and Administration (2.1), Warnings and Precautions (5.1)].

- Strongly advise patients and caregivers to always use the enclosedgraduated oral syringe or dosing cup when administering Oxycodone Hydrochloride Oral Solution to correctly measure the prescribed amount of medication [see Warnings and Precautions (5.1)] .
- Instruct patients and caregivers to never use household teaspoons or tablespoons to measure Oxycodone Hydrochloride Oral Solution.
- Advise patients and caregivers not to adjust the dose of Oxycodone Hydrochloride Oral Solution without consulting with a physician or other healthcare provider.

Important Discontinuation Instructions

In order to avoid developing withdrawal symptoms, instruct patients not to discontinue Oxycodone Hydrochloride Oral Solution without first discussing a tapering plan with the prescriber [see Dosage and Administration (2.5)].

Driving or Operating Heavy Machinery

Inform patients that Oxycodone Hydrochloride Oral Solution may impair the ability to perform potentially hazardous activities such as driving a car or operating heavy machinery. Advise patients not to perform such tasks until they know how they will react to the medication [see Warnings and Precautions (5.16)].

Constipation

Advise patients of the potential for severe constipation, including management instructions and when to seek medical attention [see Adverse Reactions (6), Clinical Pharmacology (12.2)].

Adrenal Insufficiency

Inform patients that opioids could cause adrenal insufficiency, a potentially life-threatening condition. Adrenal insufficiency may present with non-specific symptoms and signs such as nausea, vomiting, anorexia, fatigue, weakness, dizziness, and low blood pressure. Advise patients to seek medical attention if they experience a constellation of these symptoms [see Warnings and Precautions (5.10)].

Hypotension

Inform patients that Oxycodone Hydrochloride Oral Solution may cause orthostatic hypotension and syncope. Instruct patients how to recognize symptoms of low blood pressure and how to reduce the risk of serious consequences should hypotension occur (e.g., sit or lie down, carefully rise from a sitting or lying position) [see Warnings and Precautions (5.11)].

Anaphylaxis

Inform patients that anaphylaxis has been reported with ingredients contained in Oxycodone Hydrochloride Oral Solution. Advise patients how to recognize such a reaction and when to seek medical attention [see Adverse Reactions (6)].

Pregnancy

Neonatal Opioid Withdrawal Syndrome

Inform female patients of reproductive potential that use of Oxycodone Hydrochloride Oral Solution for an extended period of time during pregnancy can result in neonatal opioid withdrawal syndrome, which may be life-threatening if not recognized and treated [see Warnings and Precautions (5.5), Use in Specific Populations (8.1)].

Embryo-Fetal Toxicity

Inform female patients of reproductive potential that Oxycodone Hydrochloride Oral Solution can cause fetal harm and to inform the healthcare provider of a known or suspected pregnancy [see Use in Specific Populations (8.1)].

Lactation

Advise breastfeeding women using Oxycodone Hydrochloride Oral Solution to carefully observe infants for increased sleepiness (more than usual), breathing difficulties, or limpness. Instruct breastfeeding women to seek immediate medical care if they notice these signs [see Use in Specific Populations (8.2)].

Infertility

Inform patients that chronic use of opioids for an extended period of time may cause reduced fertility. It is not known whether these effects on fertility are reversible [see Use in Specific Populations (8.3)].

Manufactured by and Distributed by:
Genus Lifesciences Inc.
514 North 12th Street,
Allentown, PA 18102

Revision: April 2024

Medication Guide
Oxycodone Hydrochloride (ox-ee-CO-dohn) CII
Oral Solution

Oxycodone Hydrochloride Oral Solution is:

- A strong prescription pain medicine that contains an opioid (narcotic) that is used to manage pain severe enough to require an opioid pain medicine, when other pain treatments such as non-opioid pain medicines do not treat your pain well enough or you cannot tolerate them.
- An opioid pain medicine that can put you at risk for overdose and death. Even if you take your dose correctly as prescribed you are at risk for opioid addiction, abuse, and misuse that can lead to death.

Important information about Oxycodone Hydrochloride Oral Solution:

- Get emergency help or call 911 right away if you take too much Oxycodone Hydrochloride Oral Solution (overdose). When you first start taking Oxycodone Hydrochloride Oral Solution, when your dose is changed, or if you take too much (overdose), serious or life-threatening breathing problems that can lead to death may occur. Talk to your healthcare provider about naloxone, a medicine for the emergency treatment of an opioid overdose.
- Taking Oxycodone Hydrochloride Oral Solution with other opioid medicines, benzodiazepines, alcohol, or other central nervous system depressants (including street drugs) can cause severe drowsiness, decreased awareness, breathing problems, coma, and death.
- Never give anyone else your Oxycodone Hydrochloride Oral Solution. They could die from taking it. Selling or giving away Oxycodone Hydrochloride Oral Solution is against the law.
- Store Oxycodone Hydrochloride Oral Solution securely, out of sight and reach of children, and in a location not accessible by others, including visitors to the home.

Do not take Oxycodone Hydrochloride Oral Solution if you have:

- severe asthma, trouble breathing, or other lung problems.
- a bowel blockage or have narrowing of the stomach or intestines.
- an allergy to oxycodone or any of the ingredients in Oxycodone Hydrochloride Oral Solution.

Before taking Oxycodone Hydrochloride Oral Solution, tell your healthcare provider if you have a history of:

- head injury, seizures
- problems urinating

- liver, kidney, thyroid problems
- pancreas or gallbladder problems

- abuse of street or prescription drugs, alcohol addiction, opioid overdose, or mental health problems.

Tell your healthcare provider if you are:

- noticing your pain getting worse.If your pain gets worse after you take Oxycodone Hydrochloride Oral Solution, do not take more of Oxycodone Hydrochloride Oral Solution without first talking to your healthcare provider. Talk to your healthcare provider if the pain that you have increases, if you feel more sensitive to pain, or if you have new pain after taking Oxycodone Hydrochloride Oral Solution.
- pregnant or planning to become pregnant.Use of Oxycodone Hydrochloride Oral Solution for an extended period of time during pregnancy can cause withdrawal symptoms in your newborn baby that could be life-threatening if not recognized and treated.
- breastfeeding.Oxycodone Hydrochloride Oral Solution passes into breast milk and may harm your baby. Carefully observe infants for increased sleepiness (more than usual), breathing difficulties, or limpness. Seek immediate medical care if you notice these signs.
- living in a household where there are small children or someone who has abused street or prescription drugs.
- taking prescription or over-the-counter medicines, vitamins, or herbal supplements. Taking Oxycodone Hydrochloride Oral Solution with certain other medicines can cause serious side effects that could lead to death.

When taking Oxycodone Hydrochloride Oral Solution:

- Do not change your dose. Take Oxycodone Hydrochloride Oral Solution exactly as prescribed by your healthcare provider. Use the lowest dose possible for the shortest time needed.
- For acute (short-term) pain, you may only need to take Oxycodone Hydrochloride Oral Solution for a few days. You may have some Oxycodone Hydrochloride Oral Solution left over that you did not use. See disposal information at the bottom of this section for directions on how to safely throw away (dispose of) your unused Oxycodone Hydrochloride Oral Solution.
- See the detailed Instructions for Usefor information about how to take Oxycodone Hydrochloride Oral Solution 100 mg per 5 mL (20 mg per mL).
- Always use the enclosedgraduated measuring cup that comes with Oxycodone Hydrochloride Oral Solution 5 mg per 5 mL and the enclosedgraduated oral syringe that comes with Oxycodone Hydrochloride Oral Solution 100 mg per 5 mL (20 mg per mL) to correctly measure your dose. Never use a household teaspoon or tablespoon to measure Oxycodone Hydrochloride Oral Solution.
- Take your prescribed dose every 4 to 6 hours as needed for pain. Do not take more than your prescribed dose. If you miss a dose, take your next dose at your usual time.
- Call your healthcare provider if the dose you are taking does not control your pain.
- If you have been taking Oxycodone Hydrochloride Oral Solution regularly, do not stop taking Oxycodone Hydrochloride Oral Solution without talking to your healthcare provider.
- Dispose of expired, unwanted, or unused Oxycodone Hydrochloride Oral Solution by promptly flushing down the toilet, if a drug take-back option is not readily available. Visit www.fda.gov/drugdisposalfor additional information on disposal of unused medicines.

While taking Oxycodone Hydrochloride Oral Solution DO NOT:

- Drive or operate heavy machinery, until you know how Oxycodone Hydrochloride Oral Solution affects you. Oxycodone Hydrochloride Oral Solution can make you sleepy, dizzy, or lightheaded.
- Drink alcohol or use prescription or over-the-counter medicines that contain alcohol. Using products containing alcohol during treatment with Oxycodone Hydrochloride Oral Solution may cause you to overdose and die.

The possible side effects of Oxycodone Hydrochloride Oral Solution:

- constipation, nausea, sleepiness, vomiting, tiredness, headache, dizziness, abdominal pain. Call your healthcare provider if you have any of these symptoms and they are severe.

Get emergency medical help or call 911 right away if you have:

- trouble breathing, shortness of breath, fast heartbeat, chest pain, swelling of your face, tongue, or throat, extreme drowsiness, light-headedness when changing positions, feeling faint, agitation, high body temperature, trouble walking, stiff muscles, or mental changes such as confusion.

These are not all the possible side effects of Oxycodone Hydrochloride Oral Solution. Call your healthcare provider for medical advice about side effects. You may report side effects to FDA at 1-800-FDA-1088. For more information go to dailymed.nlm.nih.gov
Manufactured by and Distributed by:
Genus Lifesciences Inc., 514 North 12thStreet, Allentown, PA 18102 , www.genuslifesciences.comor call 1-866-511-6754.

This Medication Guide has been approved by the U.S. Food and Drug Administration.
Issued: 12/2023

Patient Instructions for Use

Oxycodone Hydrochloride Oral Solution 100 mg per 5 mL (20 mg per mL) Oral Syringe
Important information about measuring Oxycodone Hydrochloride Oral Solution

- Always use the oral syringe provided with your Oxycodone Hydrochloride Oral Solution to make sure you measure the right amount.
- Measure the dose of medicine from the widest part of the plunger. Do not measure from the narrow tip. See Figure 1.

Step 1.Insert the tip of the oral syringe into the medicine bottle.
Step 2.Pull back the plunger to the line that matches the dose prescribed by your healthcare provider.
Step 3.Remove the oral syringe from the medicine bottle.
Step 4.Take your medicine by slowly pushing the plunger until the oral syringe is empty.

Figure 1

PRINCIPAL DISPLAY PANEL - 30 mL Bottle Label

NDC 64950-353-03

Oxycodone
Hydrochloride
Oral Solution
CII

100 mg/5 mL
20 mg/mL

ONLY FOR USE IN PATIENTS WHO ARE
OPIOID TOLERANT

Rx Only
30 mL

Genus
Lifesciences Inc.

PRINCIPAL DISPLAY PANEL - 500 mL Bottle Label

NDC 64950-354-50

Oxycodone
Hydrochloride
Oral Solution, USP
CII

5 mg per 5 mL
(1 mg/mL)

Rx Only
500 mL

Genus
Lifesciences Inc.

PRINCIPAL DISPLAY PANEL - 5 mL Cup Label

NDC 64950-354-05

Oxycodone Hydrochloride
Oral Solution, USP
CII

5 mg/5 mL
(1 mg/mL)

See package insert for
dosing information.

5 mL

Genus Lifesciences Inc.
Allentown, PA 18102

Rev. 3/21

Rx Only